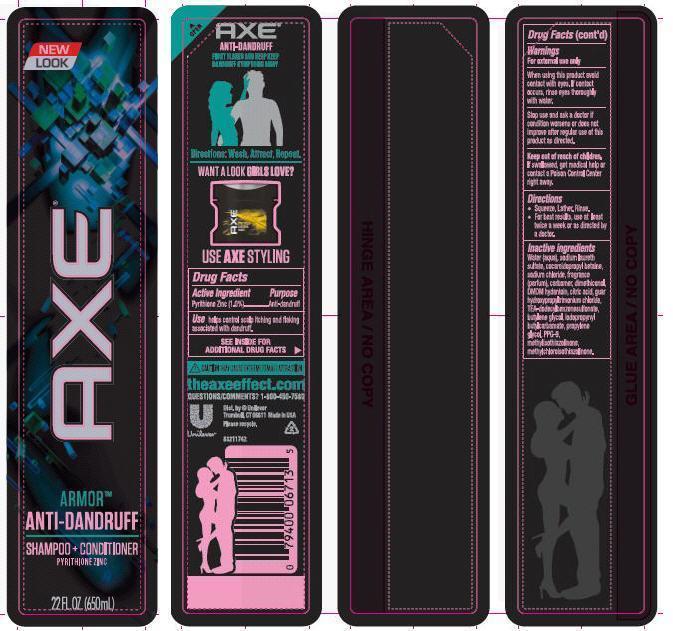 DRUG LABEL: Axe
NDC: 64942-1302 | Form: SHAMPOO
Manufacturer: Conopco Inc. d/b/a Unilever
Category: otc | Type: HUMAN OTC DRUG LABEL
Date: 20130604

ACTIVE INGREDIENTS: Pyrithione Zinc 1 g/100 mL
INACTIVE INGREDIENTS: WATER; SODIUM LAURETH SULFATE; COCAMIDOPROPYL BETAINE; SODIUM CHLORIDE; CARBOMER HOMOPOLYMER TYPE C; DMDM HYDANTOIN; GUAR HYDROXYPROPYLTRIMONIUM CHLORIDE (1.7 SUBSTITUENTS PER SACCHARIDE); TRIETHANOLAMINE DODECYLBENZENESULFONATE; 1,3-BUTYLENE GLYCOL; CITRIC ACID MONOHYDRATE; IODOPROPYNYL BUTYLCARBAMATE; PROPYLENE GLYCOL; METHYLCHLOROISOTHIAZOLINONE; METHYLISOTHIAZOLINONE; PPG-9

Axe 2 in 1 Armor Anti-Dandruff Shampoo

Active Ingredient
Pyrithione Zinc (1.0%)

PURPOSE

PurposeAnti-dandruff

INDICATIONS AND USAGE

Usehelps control scalp itching and flaking associated with dandruff.

Warnings
For external use only

When using this product avoid contact with eyes. If contact occurs, rinse eyes thoroughly with water.

Stop use and ask a doctor if condition worsens or does not improve after regular use of this product as directed.

Keep out of reach of children. If swallowed, get medical help or contact a Poison Control Center right away.

DOSAGE AND ADMINISTRATION

Directions· Squeeze. Lather. Rinse.
· For best results, use at least twice a week or as directed by a doctor.

Inactive ingredients
Water (Aqua), sodium laureth sulfate, cocamidopropyl betaine, sodium chloride, fragrance (parfum), carbomer, dimethiconol, DMDM hydantoin, citric acid, guar hydroxypropyltrimonium chloride, TEA-dodecylbenzenesulfonate, butylene glycol, iodopropynyl butylcarbamate, propylene glycol, PPG-9, methylchloroisothiazolinone, Methylisothiazolinone.

QUESTIONS

theaxeeffect.com
QUESTIONS/COMMENTS?
1-800-450-7580